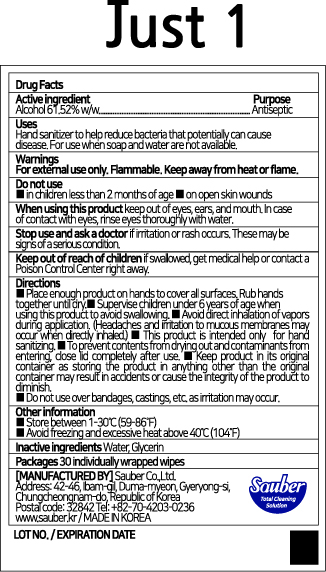 DRUG LABEL: Just 1
NDC: 78880-062 | Form: CLOTH
Manufacturer: Sauber Co.,Ltd.
Category: otc | Type: HUMAN OTC DRUG LABEL
Date: 20200629

ACTIVE INGREDIENTS: ALCOHOL 0.6152 1/1 1
INACTIVE INGREDIENTS: GLYCERIN; WATER

Just 1 | 30 ct. in 1 BOX | 78880-062-30 | HAND SANITIZING WIPES